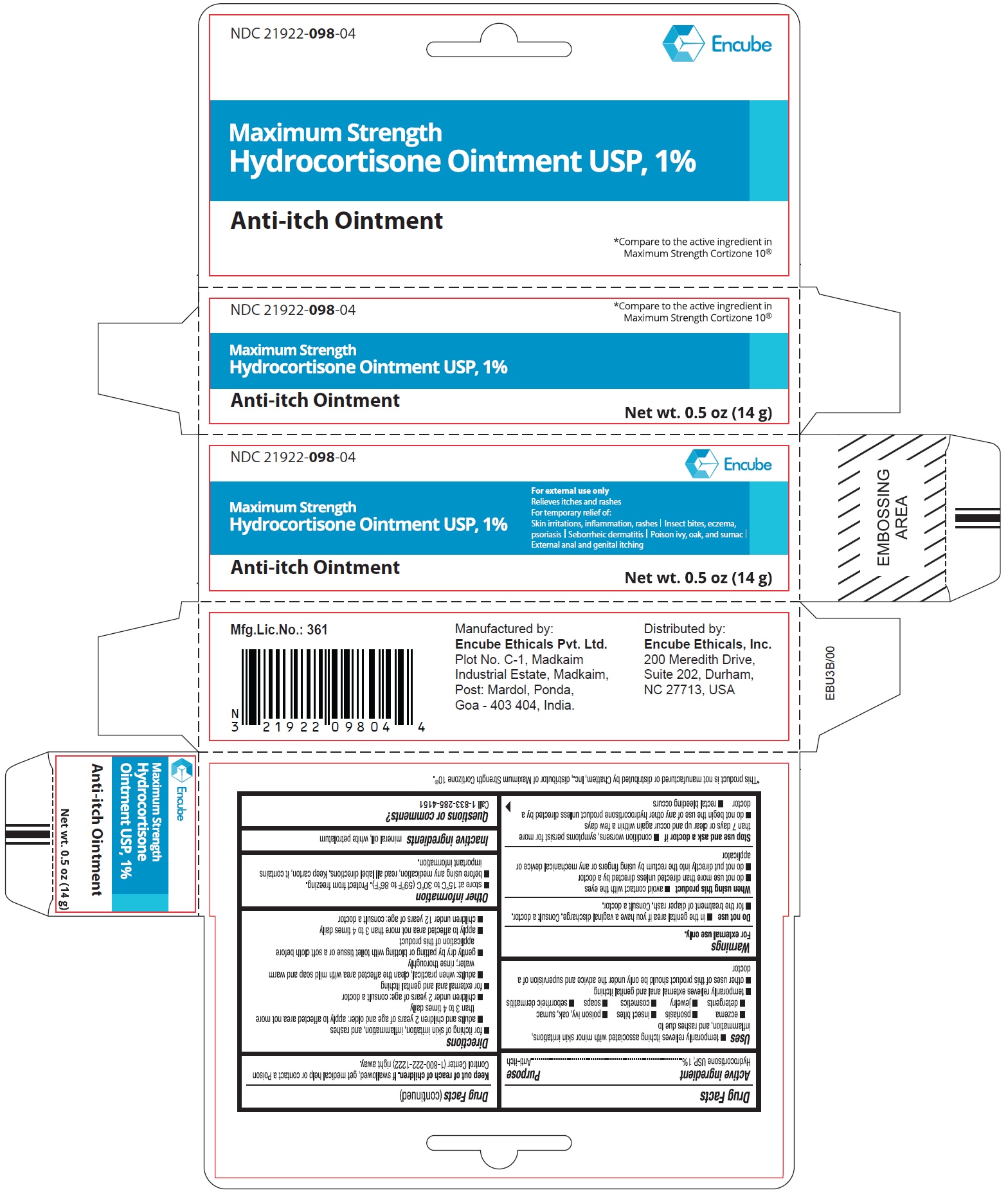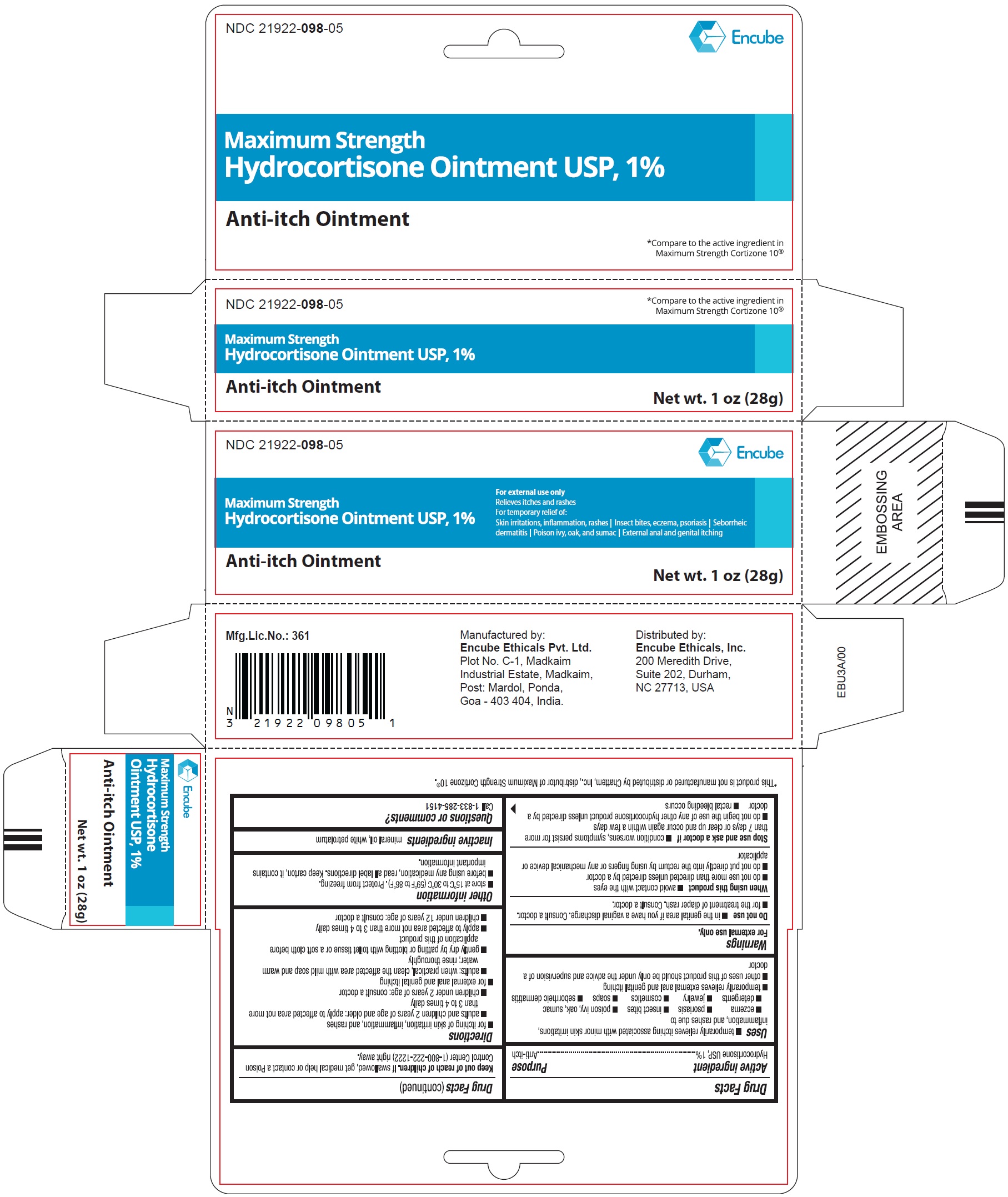 DRUG LABEL: Hydrocortisone
NDC: 21922-098 | Form: OINTMENT
Manufacturer: Encube Ethicals, Inc.
Category: otc | Type: HUMAN OTC DRUG LABEL
Date: 20250909

ACTIVE INGREDIENTS: HYDROCORTISONE 1 g/100 g
INACTIVE INGREDIENTS: MINERAL OIL; PETROLATUM

Hydrocortisone Ointment 1%

ACTIVE INGREDIENT(S)

Hydrocortisone USP, 1%

PURPOSE

Anti-itch

USE(S)

■ temporarily relieves itching associated with minor skin irritations, inflammation, and rashes due to

■ eczema ■ psoriasis ■ insect bites ■ poison ivy, oak, sumac

■ detergents ■ jewelry ■ cosmetics ■ soaps ■ seborrheic dermatitis

■ temporarily relieves external anal and genital itching

■ other uses of this product should be only under the advice and supervision of a doctor

WARNINGS

For external use only.

DO NOT USE

■ in the genital area if you have a vaginal discharge. Consult a doctor.

■ for the treatment of diaper rash. Consult a doctor.

WHEN USING THIS PRODUCT

■ avoid contact with the eyes

■ do not use more than directed unless directed by a doctor

■ do not put directly into the rectum by using fingers or any mechanical device or applicator

STOP USE AND ASK DOCTOR IF

■ condition worsens, symptoms persist for more than 7 days or clear up and occur again within a few days

■ do not begin the use of any other hydrocortisone product unless directed by a doctor

■ rectal bleeding occurs

KEEP OUT OF REACH OF CHILDREN

If swallowed, get medical help or contact a Poison Control Center (1-800-222-1222) right away.

DIRECTIONS

■ for itching of skin irritation, inflammation, and rashes

■ adults and children 2 years of age and older: apply to affected area not more than 3 to 4 times daily

■ children under 2 years of age: consult a doctor

■ for external anal and genital itching

■ adults: when practical, clean the affected area with mild soap and warm water; rinse thoroughly

■ gently dry by patting or blotting with toilet tissue or a soft cloth before application of this product

■ apply to affected area not more than 3 to 4 times daily

■ children under 12 years of age: consult a doctor

OTHER INFORMATION

■ store at 15°C to 30°C (59°F to 86°F) Protect from freezing.

■ before using any medication, read all label directions. Keep carton, it contains important information.

INACTIVE INGREDIENTS

mineral oil, white petrolatum

QUESTIONS OR COMMENTS?

Call 1-833-285-4151

PRINCIPAL DISPLAY PANEL

Hydrocortisone Ointment USP, 1%

Anti-itch ointment

Net wt. 0.5 oz (14g)

Hydrocortisone Ointment USP, 1%

Anti-itch ointment

Net wt. 1 oz (28g)